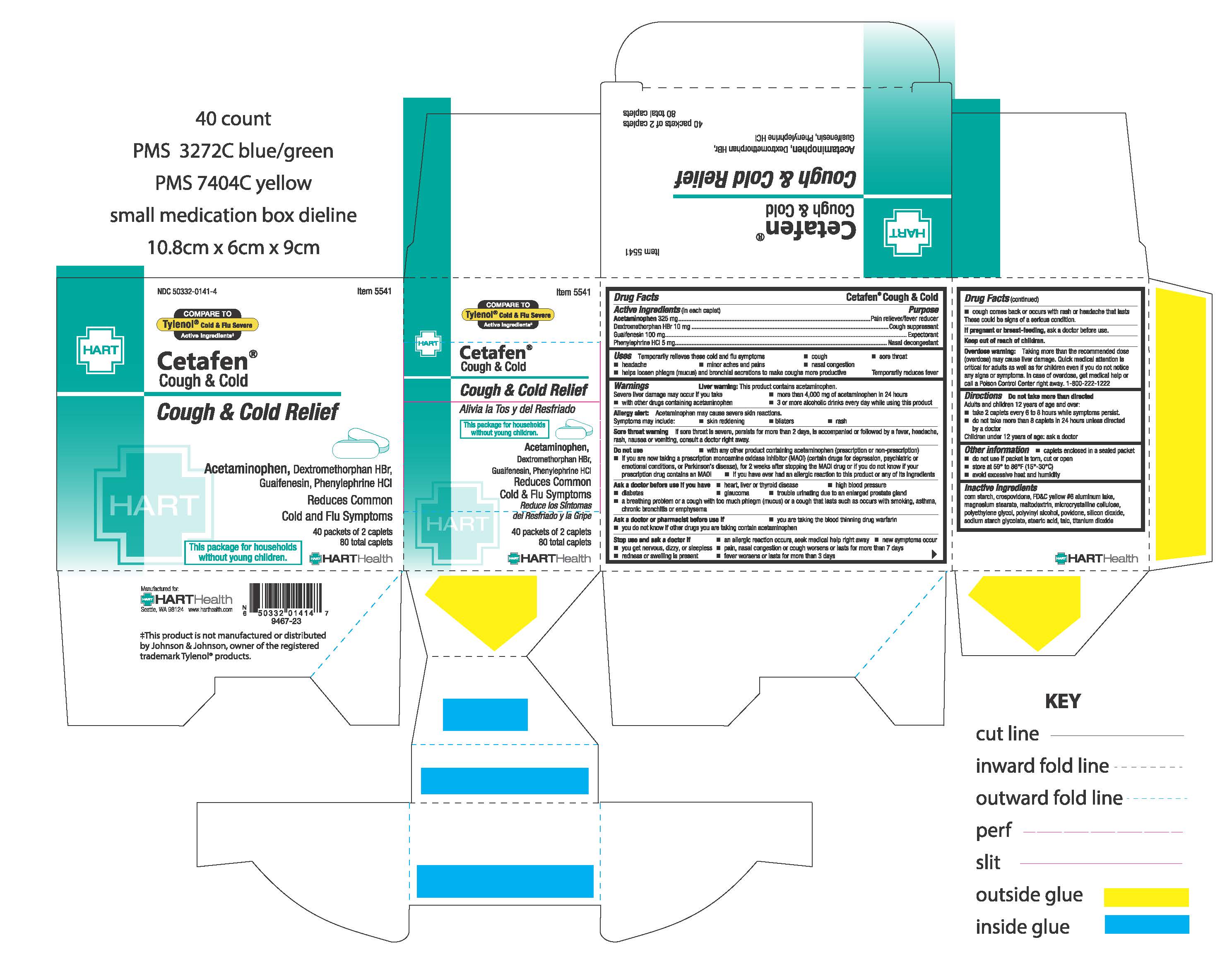 DRUG LABEL: CETAFEN COUGH and COLD
NDC: 50332-0141 | Form: TABLET, FILM COATED
Manufacturer: HART Health
Category: otc | Type: HUMAN OTC DRUG LABEL
Date: 20251224

ACTIVE INGREDIENTS: GUAIFENESIN 100 mg/1 1; PHENYLEPHRINE HYDROCHLORIDE 5 mg/1 1; ACETAMINOPHEN 325 mg/1 1; DEXTROMETHORPHAN HYDROBROMIDE 10 mg/1 1
INACTIVE INGREDIENTS: MICROCRYSTALLINE CELLULOSE; TALC; POLYVINYL ALCOHOL, UNSPECIFIED; CROSPOVIDONE; FD&C YELLOW NO. 6; POLYETHYLENE GLYCOL, UNSPECIFIED; POVIDONE; SILICON DIOXIDE; MALTODEXTRIN; STARCH, CORN; MAGNESIUM STEARATE; SODIUM STARCH GLYCOLATE TYPE A POTATO; TITANIUM DIOXIDE; STEARIC ACID

CETAFEN COUGH and COLD

Active ingredients (in each caplet)

Acetaminophen 325 mg

Dextromethorphan HBr 10 mg

Guaifenesin 100 mg

Phenylephrine HCl 5 mg

Purpose

Pain reliever/fever reducer

Cough suppressant

Expectorant

Nasal decongestant

Uses

Temporarily relieves these cold and flu symptoms

- cough
- sore throat
- headache
- minor aches and pains
- nasal congestion
- sinus congestion and pressure
- helps loosen phlegm (mucus) and bronchial secretions to coughs more productive

Temporarily reduces fever

Warnings

Liver warning: This product contains acetaminophen. Severe liver damage may occur if you take:

- more than 4,000 mg of acetaminophen in 24 hours
- with other drugs containing acetaminophen
- 3 or more alcoholic drinks every day while using this product

Allergy alert: Acetaminophen may cause severe skin reactions. Symptoms may include:

- skin reddening
- blisters
- rash

Sore throat warning: If sore throat is severe, persists for more than 2 days, is accompanied or followed by fever, headache, rash, nausea, or vomiting, consult a doctor right away.

Do not use

- with any other drug containing acetaminophen (prescription or nonprescription)
- if you have ever had an allergic reaction to this product or any of its ingredients
- if you are now taking a prescription monoamine oxidase inhibitor (MAOI) (certain drugs for depression, psychiatric or emotional conditions, or Parkinson’s disease), or for 2 weeks after stopping the MAOI drug, or if you do not know if your prescription drug contains an MAOI

Ask a doctor before use if you have

- heart, liver, or thyroid disease
- high blood pressure
- diabetes
- glaucoma
- trouble urinating due to an enlarged prostate
- a breathing problem or a cough with too much phlegm (mucus) or a cough that lasts as occurs with smoking, asthma, chronic bronchitis, or emphysema

Ask a doctor or pharmacist before use if

- you are taking the blood thinning drug warfarin
- you do not know if other drugs you are taking contain acetaminophen

Stop use and ask a doctor if

- an allergic reaction occurs, seek medical help right away
- redness or swelling is present
- you get nervous, dizzy, or sleepless
- new symptoms occur
- fever worsens or lasts more than 3 days
- pain, nasal congestion, or cough worsens or lasts more than 7 days
- cough comes back or occurs with a rash or headache that lasts

These could be signs of a serious condition.

PREGNANCY OR BREAST FEEDING

If pregnant or breast-feeding, ask a health professional before use.

Keep out of reach of children.

OVERDOSAGE

Overdose warning: Taking more than the recommended dose (overdose) may cause liver damage. Quick medical attention is critical for adults as well as for children even if you do notice any signs or symptoms. In case of overdose, get medical help or contact a Poison Control Center right away. 1-800-222-1222

Directions

Do not take more than directed

Adults and children 12 years of age and over

- take 2 caplets every 6 to 8 hours while symptoms persist
- do not take more than 8 caplets in 24 hours unless directed by a doctor

Children under 12 years of age: ask a doctor

Other information:

- caplets enclosed in a sealed packet
- do not use if packet is torn, cut or open
- store at 59° to 86°F (15°-30°C)
- avoid excessive heat and humidity

INACTIVE INGREDIENT

Inactive ingredients corn starch, crospovidone, FD&C yellow # 6 aluminum lake, magnesium stearate, maltodextrin, microcrystalline cellulose, polyethylene glycol, polyvinyl alcohol, povidone,silicon dioxide, sodium starch glycolate, stearic acid, talc, titanium dioxide